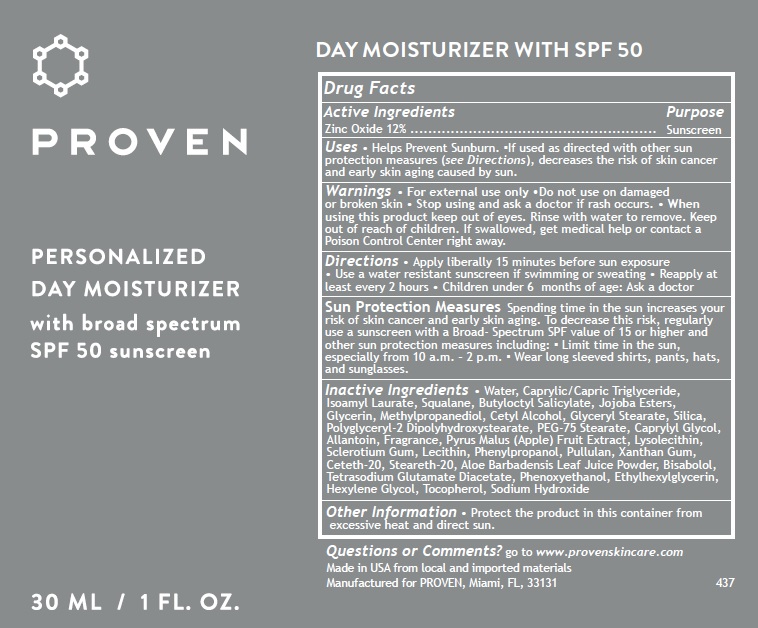 DRUG LABEL: Personalized Day Moisturizer with SPF 50
NDC: 73572-007 | Form: CREAM
Manufacturer: Proven Skincare
Category: otc | Type: HUMAN OTC DRUG LABEL
Date: 20231110

ACTIVE INGREDIENTS: ZINC OXIDE 120 mg/1 mL
INACTIVE INGREDIENTS: WATER; MEDIUM-CHAIN TRIGLYCERIDES; ISOAMYL LAURATE; SQUALANE; BUTYLOCTYL SALICYLATE; GLYCERIN; METHYLPROPANEDIOL; CETYL ALCOHOL; GLYCERYL MONOSTEARATE; SILICON DIOXIDE; POLYGLYCERYL-2 DIPOLYHYDROXYSTEARATE; PEG-75 STEARATE; CAPRYLYL GLYCOL; ALLANTOIN; APPLE; BETASIZOFIRAN; PHENYLPROPANOL; PULLULAN; XANTHAN GUM; CETETH-20; STEARETH-20; ALOE VERA LEAF; LEVOMENOL; TETRASODIUM GLUTAMATE DIACETATE; PHENOXYETHANOL; ETHYLHEXYLGLYCERIN; HEXYLENE GLYCOL; TOCOPHEROL; SODIUM HYDROXIDE

Personalized Day Moisturizer with SPF 50

Active Ingredients

Zinc Oxide 12%

Purpose

Sunscreen

Uses

• Helps Prevent Sunburn. ▪If used as directed with other sun protection measures (see Directions), decreases the risk of skin cancer and early skin aging caused by sun.

Warnings

- For external use only

Do not use

- on damaged or broken skin

Stop using and ask a doctor

- if rash occurs.

When using this product

- keep out of eyes. Rinse with water to remove.

Keep out of reach of children.

If swallowed, get medical help or contact a Poison Control Center right away.

Directions

• Apply liberally 15 minutes before sun exposure • Use a water resistant sunscreen if swimming or sweating • Reapply at least every 2 hours • Children under 6 months of age: Ask a doctor

Spending time in the sun increases your risk of skin cancer and early skin aging. To decrease this risk, regularly use a sunscreen with a Broad- Spectrum SPF value of 15 or higher and other sun protection measures including: ▪ Limit time in the sun, especially from 10 a.m. – 2 p.m. ▪ Wear long sleeved shirts, pants, hats, and sunglasses. Sun Protection Measures

Inactive Ingredients

• Water, Caprylic/Capric Triglyceride, Isoamyl Laurate, Squalane, Butyloctyl Salicylate, Jojoba Esters, Glycerin, Methylpropanediol, Cetyl Alcohol, Glyceryl Stearate, Silica, Polyglyceryl-2 Dipolyhydroxystearate, PEG-75 Stearate, Caprylyl Glycol, Allantoin, Fragrance, Pyrus Malus (Apple) Fruit Extract, Lysolecithin, Sclerotium Gum, Lecithin, Phenylpropanol, Pullulan, Xanthan Gum, Ceteth-20, Steareth-20, Aloe Barbadensis Leaf Juice Powder, Bisabolol, Tetrasodium Glutamate Diacetate, Phenoxyethanol, Ethylhexylglycerin, Hexylene Glycol, Tocopherol, Sodium Hydroxide

Other Information

• Protect the product in this container from excessive heat and direct sun.

Questions or Comments?

go to www.provenskincare.com Made in USA from local and imported materials Manufactured for PROVEN, Miami, FL, 33131